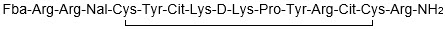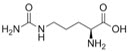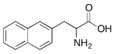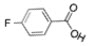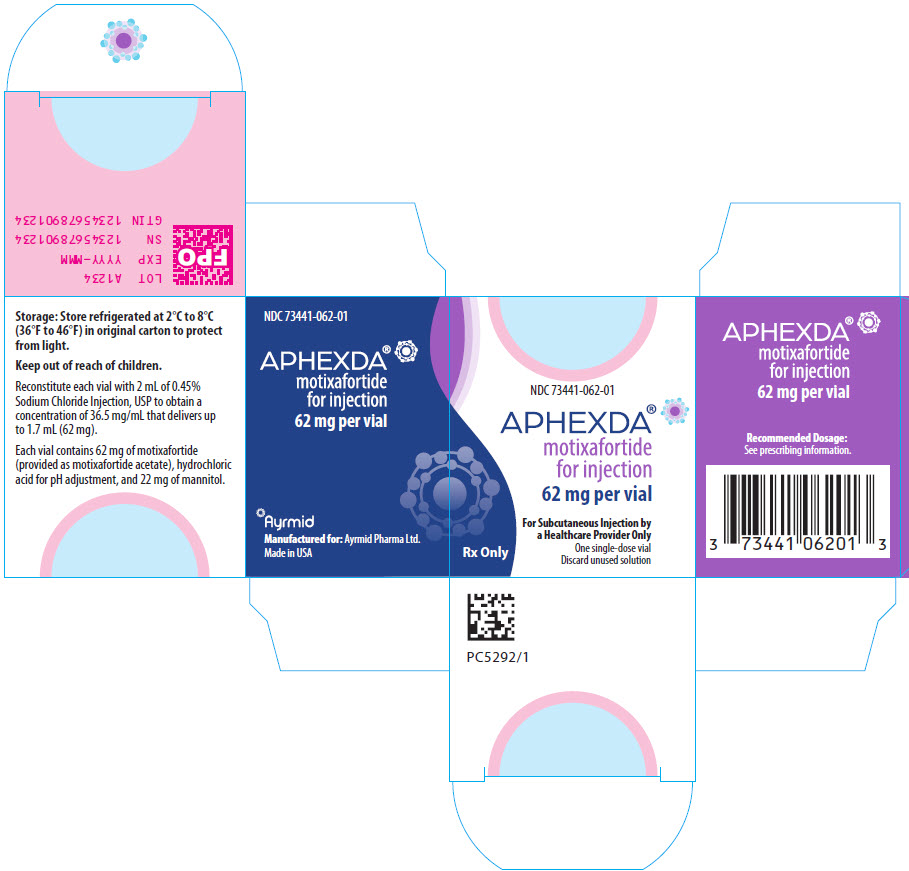 DRUG LABEL: APHEXDA
NDC: 73441-062 | Form: INJECTION, POWDER, LYOPHILIZED, FOR SOLUTION
Manufacturer: Gamida Cell Inc.
Category: prescription | Type: HUMAN PRESCRIPTION DRUG LABEL
Date: 20251028

ACTIVE INGREDIENTS: MOTIXAFORTIDE ACETATE 62 mg/1.7 mL
INACTIVE INGREDIENTS: MANNITOL; HYDROCHLORIC ACID

HIGHLIGHTS OF PRESCRIBING INFORMATION

These highlights do not include all the information needed to use APHEXDA safely and effectively. See full prescribing information for APHEXDA.
APHEXDA® (motixafortide) for injection, for subcutaneous use
Initial U.S. Approval: 2023

1 INDICATIONS AND USAGE

APHEXDA, a hematopoietic stem cell mobilizer, is indicated in combination with filgrastim (G-CSF) to mobilize hematopoietic stem cells to the peripheral blood for collection and subsequent autologous transplantation in patients with multiple myeloma. (1)

2 DOSAGE AND ADMINISTRATION

- Initiate APHEXDA treatment after filgrastim has been administered daily for 4 days. (2.1)
- Recommended dosage is 1.25 mg/kg actual body weight by subcutaneous injection 10 to 14 hours prior to initiation of apheresis. (2.2)
- A second dose of APHEXDA can be administered 10 to 14 hours prior to a third apheresis. (2.2)
- See Full Prescribing Information for instructions on preparation and administration.

3 DOSAGE FORMS AND STRENGTHS

For Injection: 62 mg as a lyophilized powder in a single-dose vial for reconstitution. (3)

4 CONTRAINDICATIONS

History of serious hypersensitivity reaction to APHEXDA. (4)

5 WARNINGS AND PRECAUTIONS

- Anaphylactic Shock and Hypersensitivity Reactions: Premedicate all patients with a combination of an H1-antihistamine, an H2 blocker, and a leukotriene inhibitor prior to each APHEXDA dose. Administer APHEXDA in a setting where personnel and therapies are available for immediate treatment. Observe for signs and symptoms and manage promptly. (2.1, 2.3, 5.1)
- Injection Site Reactions: The addition of analgesic premedication (e.g., acetaminophen) is recommended. (5.2)
- Tumor Cell Mobilization in Patients with Leukemia: APHEXDA may mobilize leukemic cells and should not be used in leukemia patients. (5.3)
- Leukocytosis: Increased circulating leukocytes have been observed. Monitor white blood cell counts during APHEXDA use. (5.4)
- Potential for Tumor Cell Mobilization: Tumor cells may be released from marrow during HSC mobilization with APHEXDA and filgrastim. Effect of reinfusion of tumor cells is unknown. (5.5)
- Embryo-fetal Toxicity: Can cause fetal harm. Advise women of reproductive potential of the potential risk to a fetus and to use effective contraception. (5.6, 8.1, 8.3)

6 ADVERSE REACTIONS

Most common adverse reactions (incidence >20%) are injection site reactions, injection site pain, injection site erythema, injection site pruritus, pruritus, flushing, and back pain. (6.1)

To report SUSPECTED ADVERSE REACTIONS, contact Gamida Cell at (844) 477-7478 or FDA at 1-800-FDA-1088 or www.fda.gov/medwatch.

8 USE IN SPECIFIC POPULATIONS

Lactation: Advise not to breastfeed. (8.2)

FULL PRESCRIBING INFORMATION

1 INDICATIONS AND USAGE

APHEXDA is indicated in combination with filgrastim (G-CSF) to mobilize hematopoietic stem cells to the peripheral blood for collection and subsequent autologous transplantation in patients with multiple myeloma.

2 DOSAGE AND ADMINISTRATION

2.1 Important Dosing Information

- Premedicate all patients before each dose of APHEXDA to reduce the risk of hypersensitivity and injection site reactions:
  - Administer diphenhydramine (12.5 mg intravenously or 25 mg to 50 mg orally, or another H1-antihistamine), an H2 blocker (e.g., famotidine), and a leukotriene inhibitor (e.g., montelukast) approximately 30 to 60 minutes before injection of APHEXDA.
  - The addition of an analgesic medication (e.g., acetaminophen) to the premedication regimen is recommended.
- Administer filgrastim 10 mcg/kg subcutaneously once daily for 4 days prior to the first dose of APHEXDA and on each day prior to each apheresis.

2.2 Recommended Dosage

The recommended dosage of APHEXDA is 1.25 mg/kg administered via slow (approximately 2 minutes) subcutaneous injection 10 to 14 hours prior to the initiation of the first apheresis. Dosing is based on actual body weight.

A second dose of APHEXDA can be administered 10 to 14 hours before a third apheresis, if necessary.

2.3 Preparation and Administration

Use aseptic technique to prepare and administer APHEXDA:

- More than one vial may be needed for a full dose. Calculate the dose, the total volume of reconstituted APHEXDA solution required, and number of APHEXDA vials required based on patient's actual body weight.
- Remove the APHEXDA vial(s) from the refrigerator and allow to reach room temperature at 20°C to 25°C (68°F to 77°F) for at least 30 minutes.
- Reconstitute each vial with 2 mL of 0.45% Sodium Chloride Injection, USP at room temperature (20°C to 25°C (68°F to 77°F)) resulting in a concentration of 36.5 mg/mL of APHEXDA and permitting withdrawal of up to 1.7 mL (62 mg). Alternatively, you can reconstitute each vial with 1 mL of Sterile Water for Injection, USP and 1 mL of 0.9% Sodium Chloride Injection, USP.
- Gently swirl and invert for up to 3 minutes slowly until completely dissolved.
- Inspect the reconstituted solution for discoloration and particulate matter. The reconstituted solution should appear clear and colorless. Do not use if the reconstituted solution is discolored, is cloudy, or contains visible particulates.
- If needed, store the reconstituted APHEXDA solution refrigerated at 2°C to 8°C (36°F to 46°F) or at room temperature at 20°C to 25°C (68°F to 77°F) for up to 24 hours protected from light.
- Withdraw the required injection volume of APHEXDA from the vial(s) into an appropriately sized syringe.
- Each injection volume should not exceed 2 mL. Divide doses requiring greater than 2 mL into multiple syringes to allow different injection sites.

Administration

- Administer subcutaneous injection into the abdomen, the back or side of the upper arms, or the thighs. Rotate injection sites. An injection should never be given into scar tissue or areas that are reddened, inflamed, or swollen. If injecting into the abdomen, avoid a 5 cm diameter circle around the navel. If more than one injection is needed for a single dose of APHEXDA, the injection sites should be at least 2 cm apart from previous injection locations. Discard unused portion of the drug.
- Monitor patients for one hour after administration [see Warnings and Precautions (5.1)].

3 DOSAGE FORMS AND STRENGTHS

For injection: 62 mg as a white to off-white lyophilized powder in a single-dose vial for reconstitution.

4 CONTRAINDICATIONS

APHEXDA is contraindicated in patients with a history of serious hypersensitivity reactions to motixafortide [see Warnings and Precautions (5.1)].

5 WARNINGS AND PRECAUTIONS

5.1 Anaphylactic Shock and Hypersensitivity Reactions

Anaphylactic shock occurred in 0.7% of APHEXDA-treated patients in clinical studies (n=407). The time to anaphylactic shock was between 5 minutes and 30 minutes after drug administration. Hypersensitivity reactions occurred in 7.6% of APHEXDA-treated patients in the GENESIS study. In addition, pruritus, flushing, urticaria, rash, erythema, vomiting, nausea and chills have been reported.

Premedicate all patients prior to each dose of APHEXDA 30-60 minutes prior to administration with a triple-drug premedication regimen that includes an H1-antihistamine, an H2 blocker, and a leukotriene inhibitor [see Dosage and Administration (2.1)]. Patients receiving concomitant negative chronotropic drugs (e.g., beta blockers) may be more at risk for hypotension in case of hypersensitivity reaction. When appropriate, beta blockers should be replaced with non-chronotropic drugs.

Administer APHEXDA only in a setting where personnel and therapies are immediately available for the treatment of anaphylaxis and other systemic reactions. Monitor patients for signs or symptoms of hypersensitivity reactions for one hour following administration of APHEXDA and manage reactions promptly.

5.2 Injection Site Reactions

Injection site reactions were reported in 73% of patients receiving APHEXDA in the GENESIS trial. Symptoms of injection site reactions included pain, erythema, pruritus, bruising, discomfort, induration, mass, nodule, rash, swelling, and urticaria. Among 92 patients treated with APHEXDA, the highest severity of the reactions was severe in 9%.

Premedicate with an analgesic medication (e.g., acetaminophen) prior to each APHEXDA dose. Use analgesic medication and local treatments postdose, as needed.

5.3 Tumor Cell Mobilization in Patients with Leukemia

For the purpose of hematopoietic stem cell (HSC) mobilization, APHEXDA may cause mobilization of leukemic cells and subsequent contamination of the apheresis product. Therefore, APHEXDA is not intended for HSC mobilization and harvest in patients with leukemia.

5.4 Leukocytosis

Administration of APHEXDA in conjunction with filgrastim increases circulating leukocytes as well as HSC populations. Monitor white blood cell counts during APHEXDA use.

5.5 Potential for Tumor Cell Mobilization

When APHEXDA is used in combination with filgrastim for HSC mobilization, tumor cells may be released from the marrow and subsequently collected in the leukapheresis product. The effect of potential reinfusion of tumor cells has not been well-studied.

5.6 Embryo-fetal Toxicity

Based on its mechanism of action, APHEXDA can cause fetal harm when administered to a pregnant woman. Animal models link dysfunction in CXCR4/SDF-1 signaling to adverse outcomes in mammalian embryo-fetal development and suggest risks to normal placental development.

Advise pregnant women of the potential risk to the fetus. Advise females of reproductive potential to use effective contraception during treatment with APHEXDA and for 8 days after the final dose [see Use in Specific Populations (8.1, 8.3)].

6 ADVERSE REACTIONS

The following clinically significant adverse reactions are discussed in other sections of the labeling:

- Anaphylactic Shock and Hypersensitivity Reactions [see Warnings and Precautions (5.1)]
- Injection Site Reactions [see Warnings and Precautions (5.2)]
- Potential for Tumor Cell Mobilization in Patients in Leukemia [see Warnings and Precautions (5.3)]
- Leukocytosis [see Warnings and Precautions (5.4)]
- Potential for Tumor Cell Mobilization [see Warnings and Precautions (5.5)]

6.1 Clinical Trials Experience

Because clinical trials are conducted under widely varying conditions, adverse reaction rates observed in the clinical trials of a drug cannot be directly compared to rates in the clinical trials of another drug and may not reflect the rates observed in practice.

The safety of APHEXDA was evaluated in the GENESIS study based on data from 92 patients with multiple myeloma who received at least one dose of APHEXDA 1.25 mg/kg subcutaneously and filgrastim and 42 patients who received placebo and filgrastim for mobilization of hematopoietic stem cells for collection and apheresis [see Clinical Studies (14)]. The premedication regimen changed during the conduct of the trial as evidence of hypersensitivity reactions was noted. Of the 92 patients who received at least one dose of APHEXDA, 14 patients received the triple-drug premedication regimen and 78 did not receive the triple-drug premedication regimen (either received no premedication or another premedication regimen).

Serious adverse reactions occurred in 5.4% of patients receiving APHEXDA in combination with filgrastim. Serious adverse reactions included vomiting, injection site reaction, hypersensitivity reaction, injection site cellulitis, hypokalemia and hypoxia.

One patient did not receive the 5th dose of filgrastim due to an elevated white blood cell count following administration of APHEXDA. The most common adverse reactions occurring in GENESIS (>20% and at least 2% higher than the filgrastim + placebo arm) were injection site reactions (pain, erythema and pruritus), pruritus, flushing, and back pain. Table 1 summarizes the common adverse reactions in GENESIS.

Table 1: Common Adverse Reactions in Patients with Multiple Myeloma During Hematopoietic Stem Cell Mobilization and Apheresis in GENESIS [Adverse reactions that occurred in ≥10% in APHEXDA-treated patients and ≥2% more than placebo-treated patients.]
 | APHEXDA and Filgrastim n=92 % |  | Placebo and Filgrastim n=42 %
 | All Grades | Grade ≥3 [All reactions were grade 3.] | All Grades | Grade ≥3
Injection site reactions [Injection site reactions includes: injection site bruising, injection site discomfort, injection site erythema, injection site induration, injection site mass, injection site nodule, injection site pain, injection site pruritus, injection site rash, injection site swelling, injection site urticaria, injection site cellulitis and injection related reaction.] | 73 | 8 | 5 | 0
Injection site pain | 53 | 7 | 5 | 0
Injection site erythema | 27 | 0 | 0 | 0
Injection site pruritus | 24 | 0 | 0 | 0
Pruritus | 38 | 11 | 0 | 0
Flushing [Flushing includes hot flush.] | 33 | 7 | 0 | 0
Rash [Rash includes: rash erythematous, rash maculo-papular, rash papular and rash pruritic.] | 16 | 0 | 5 | 0
Urticaria | 14 | 1.1 | 0 | 0
Erythema | 12 | 0 | 0 | 0
Back pain [Back pain includes spinal pain and sacral pain.] | 21 | 0 | 17 | 0
Paresthesia [(g) Paresthesia includes: paresthesia oral, hypoesthesia, hypoesthesia oral and burning sensation.] | 19 | 0 | 17 | 0
Hypokalemia | 15 | 4.3 | 12 | 0
Nausea | 14 | 0 | 12 | 0

Clinically relevant adverse reactions that occurred in the APHEXDA arm only in <10% of patients include dermatitis exfoliative generalized, ear swelling, pyrexia, chills, dizziness, tremor and hypertension.

6.2 Postmarketing Experience

The following adverse reactions have been identified during post approval use of APHEXDA. Because these reactions are reported voluntarily from a population of uncertain size, it is not always possible to reliably estimate their frequency or establish a causal relationship to drug exposure:

General Disorders and Administration Site Conditions – injection site necrosis, injection site ulcer.

8 USE IN SPECIFIC POPULATIONS

8.1 Pregnancy

Risk Summary

Based on its mechanism of action, APHEXDA can cause fetal harm when administered to a pregnant woman [see Clinical Pharmacology (12.1)]. There are no available data with APHEXDA use in pregnant women informing the risk of embryo-fetal toxicity. Animal models link dysfunction in CXCR4/SDF-1 signaling to adverse outcomes in mammalian embryo-fetal development and suggest risks to normal placental development (see Data). No animal studies have been conducted to evaluate the effect of motixafortide on reproduction and fetal development. Advise pregnant women of the potential risk to a fetus.

The background risk of major birth defects and miscarriages for the indicated population is unknown. In the U.S. general population, the estimated background risk of major birth defects and miscarriage in clinically recognized pregnancies is 2% to 4% and 15% to 20%, respectively.

Data

Animal Data

Animal reproduction studies have not been conducted with motixafortide to evaluate its effect on reproduction and embryo-fetal development. Disruption of CXCR4/SDF-1 signaling in mice and other models caused increased embryo-fetal lethality, and impairment of vascularization, cardiac anomalies, reduced hematopoiesis, impaired bone marrow myelopoiesis, disorganized neural layers in cerebellum, and reduced neural innervation of limbs. CXCR4/SDF-1 levels have been shown to play a key role in stimulating trophoblast proliferation and differentiation necessary for appropriate placental growth and function in humans.

8.2 Lactation

Risk Summary

There are no data on the presence of motixafortide in human milk, the effects on the breastfed child, or the effects on milk production. Because of the potential serious adverse reactions in the breastfed child, advise females that breastfeeding is not recommended during the treatment with APHEXDA and for 8 days after the final dose.

8.3 Females and Males of Reproductive Potential

Pregnancy Testing

Verify pregnancy status in females of reproductive potential prior to initiating APHEXDA.

Contraception

Females

APHEXDA can cause fetal harm when administered to pregnant women [see Use in Specific Populations (8.1)]. Advise females of reproductive potential to use effective contraception during treatment with APHEXDA and for 8 days after the final dose [see Use in Specific Populations (8.1)].

8.4 Pediatric Use

The safety and effectiveness of APHEXDA have not been established in pediatric patients.

8.5 Geriatric Use

Of the total number of patients in the GENESIS study, 33.8% were ≥65 years old, while 1.25% were ≥75 years old in the APHEXDA arm. No overall differences in safety or effectiveness were observed between these patients and younger patients.

11 DESCRIPTION

APHEXDA for injection contains motixafortide, which is a hematopoietic stem cell mobilizer. The chemical name of the synthetic motixafortide acetate, the active pharmaceutical ingredient, is N-(4-Fluoro-benzoyl)-L-arginyl-L-arginyl-[L-3-naphthyl)alanyl]-L-cysteinyl-L-tyrosyl^5-L-citrullinyl-L-lysyl-D-lysyl-L-prolyl-L-tyrosyl^10-L-arginyl-L-citrullinyl-L-cysteinyl-L-arginineamide, cyclic (4-13)-disulfide, acetate salt. Motixafortide acetate is a synthetic, cyclic peptide composed of a sequence of amino acids with the following structure:

Sequence:

Cit: Citrulline
Nal: Naphthylalanine
Fba: 4-Florobenzoic acid

Counter Ion: Acetate

Molecular weight: 2159.6 g/mol (as the free base)

APHEXDA is supplied as a sterile white to off-white, preservative-free lyophilized powder in single-dose vials. Each vial contains 73 mg of motixafortide (provided as motixafortide acetate) for reconstitution with 2 mL 0.45% saline, delivering 62 mg motixafortide per 1.7 mL. Motixafortide is present as a salt with 4 to 8.5 molar equivalents of acetate. The inactive ingredients include 26 mg of mannitol and hydrochloric acid for pH adjustment.

Reconstitution with 2 mL of 0.45% sodium chloride for injection (or 1 mL water for injection + 1 mL 0.9% sodium chloride for injection) yields a clear solution of 36.5 mg/mL motixafortide, pH 5.8 to 7.5.

12 CLINICAL PHARMACOLOGY

12.1 Mechanism of Action

Motixafortide is an inhibitor of the C-X-C Motif Chemokine Receptor 4 (CXCR4) and blocks the binding of its cognate ligand, stromal-derived factor-1α (SDF-1α)/C-X-C Motif Chemokine Ligand 12 (CXCL12).

SDF-1α and CXCR4 play a role in the trafficking and homing of human hematopoietic stem cells to the marrow compartment. Once in the marrow, stem cell CXCR4 can help anchor these cells to the marrow matrix, either directly via SDF-1α or through the induction of other adhesion molecules.

Treatment with motixafortide resulted in leukocytosis, and elevations in circulating hematopoietic stem and progenitor cells into the peripheral circulation in mice, rats, dogs, and humans.

Stem cells mobilized by motixafortide were capable of engraftment with long-term repopulating capacity in a rodent transplantation model.

12.2 Pharmacodynamics

In vitro studies showed that the concentration for half-maximal inhibition (IC50) of motixafortide towards CXCR4 ranges from 0.42 – 4.5 nM, the binding affinity (KD) is 7.9 pM and the dissociation rate (Kd) from the CXCR4 receptor is 3.38e-5 s-1 with receptor occupancy maintained over >72 hours.

The pharmacodynamics of motixafortide was evaluated in clinical studies conducted in healthy volunteers, healthy donors paired with recipients with advanced hematological malignancies, and multiple myeloma patients. Across all clinical studies, mobilization of CD34+ to peripheral blood was observed.

In healthy volunteers after administration of motixafortide as monotherapy, CD34+ cell counts increased with time, reaching maximal levels at 16 hours postdose. Thereafter, CD34+ cell counts declined slightly but remained elevated well above baseline at the last observation timepoint 24 hours postdose.

Data on the fold increase in peripheral blood CD34+ cell count (cells/mcL) by apheresis day were evaluated in the placebo-controlled part of the GENESIS study. The fold increase in CD34+ cell count over the 24-hour period, from the day prior to the first apheresis (before filgrastim administration) to the next morning before filgrastim administration (12 hours after APHEXDA administration) is summarized in Table 2.

During this 24-hour period, a single dose of motixafortide or placebo was administered 10 to 14 hours prior to apheresis.

Table 2: Fold Increase in Peripheral Blood CD34+ Cell Count following Pre-treatment with Filgrastim and Administration of APHEXDA in GENESIS
APHEXDA and Filgrastim |  | Placebo and Filgrastim
Median | Mean (SD) | Median | Mean (SD)
6.7 | 7.7 (7.5) | 1.5 | 1.6 (0.7)

Cardiac Electrophysiology

A thorough QT study in 38 healthy volunteers showed APHEXDA prolongs the QTcI interval in a concentration-dependent fashion. At 1.7-fold the Cmax of the maximum approved recommended dose (1.25 mg/kg), the mean placebo-corrected QTcI change from baseline was 11 (90% CI: 8 to 14) msec.

12.3 Pharmacokinetics

The pharmacokinetics of motixafortide were evaluated using both noncompartmental and population PK approaches in various populations, including healthy volunteers, patients with acute myeloid leukemia, and patients with multiple myeloma. Subjects received single or multiple doses ranging between 0.24 mg/kg to 2 mg/kg of APHEXDA administered by subcutaneous injections using a weight-based (mg/kg) dosing strategy as monotherapy or in combination with filgrastim with or without chemotherapy.

The PK characteristics of motixafortide following subcutaneous administration were similar across all study populations.

A population pharmacokinetic analysis was conducted using 2240 plasma motixafortide concentrations from 223 individuals, including 81 healthy subjects, 37 patients with acute myeloid leukemia, and 105 patients with multiple myeloma.

Motixafortide pharmacokinetics following subcutaneous administration were adequately described by a 3-compartment model with first-order absorption, dose-dependent relative bioavailability, and linear elimination kinetics. Minimal to no drug accumulation was observed following once daily dose administration and, as such, the single dose PK profile is considered representative of a steady state profile.

Absorption

After subcutaneous injection as either a single or repeated dose at 0.24 to 2 mg/kg, motixafortide appeared in plasma with time to maximum concentration occurring at approximately 0.25 to 1.17 hours.

Distribution

Motixafortide is highly bound to human plasma proteins (>99%). The estimated volume of distribution of the central compartment in a typical subject is 27 L.

Metabolism

Motixafortide undergoes non-specific degradation into small peptides and individual amino acids and their derivatives by catabolic pathways. Catabolism can occur in both blood and liver microsomes. In in vitro studies using human and animal biomaterials, no prominent unique human metabolites were identified.

Elimination

Motixafortide has an effective half-life in human plasma of approximately 2 hours. The elimination kinetics were similar in healthy subjects and patients with multiple myeloma.

Apparent total clearance of motixafortide for a typical subject is 46.5 L/h.

No mass balance studies were conducted in humans.

In studies conducted in rats and dogs, the total amount of ^14C-labeled motixafortide-related material excreted in urine was approximately 80% and 82%, respectively, of the dose administered and no parent drug was detected in urine. In both species, no metabolite exceeded 30% of total clearance.

Specific Populations

Renal Impairment

Based on the population PK analysis, in patients with mildly to moderately decreased renal function, the pharmacokinetic profile of motixafortide was not significantly affected. While the effect of severe renal impairment on the clearance of motixafortide has not been evaluated, a significant effect is not anticipated.

Hepatic Impairment

Motixafortide is catabolized in both the liver and blood, and animal data suggest that the main excretion pathway of its metabolites is via the kidneys and biliary excretion is minimal. Based on the population PK analysis, mildly impaired liver function did not significantly affect the pharmacokinetic profile of motixafortide. The effect of moderate to severe hepatic impairment has not been evaluated, but the risk for adverse reactions due to increased exposure is low because motixafortide is administered as a single dose.

Race/Ethnicity

In the population PK analysis, ethnicity as a covariate was not found to be a statistically significant predictor of motixafortide PK.

Gender

In the population analysis, minimal effect of gender was seen on the overall pharmacokinetic profile of motixafortide. Despite higher relative bioavailability in females compared to males, the mg/kg dosing strategy and generally lower body weights in females result in only 10% higher exposures (AUC0-24h and Cmax) in females versus males for a weight-based dose and therefore is not considered clinically meaningful.

Age

In the population PK analysis, age as a covariate was not found to be a statistically significant predictor of motixafortide PK.

Drug Interaction Studies

In vitro studies showed a lack of significant (>25%) cytochrome P450 (CYP) inhibition in human hepatocytes, a lack of CYP induction potential in human hepatocytes, and a low potential for transporter-mediated interactions. As such, motixafortide has a low potential for both metabolism- and transporter-mediated drug interactions.

12.6 Immunogenicity

The observed incidence of anti-drug antibodies is highly dependent on the sensitivity and specificity of the assay. Differences in assay methods preclude meaningful comparisons of the incidence of anti-drug antibodies between studies, including those of motixafortide.

No pre-existing or treatment-emergent (up to 8 weeks post-administration) anti-drug antibodies were detected in 84 patients with multiple myeloma who received one or two administrations of motixafortide in combination with filgrastim for hematopoietic stem cell mobilization in the GENESIS study [see Clinical Studies (14)].

13 NONCLINICAL TOXICOLOGY

13.1 Carcinogenesis, Mutagenesis, Impairment of Fertility

Carcinogenicity studies with motixafortide have not been conducted. Motixafortide was not genotoxic in an in vitro bacterial mutation assay (Ames test), in an in vitro chromosomal aberration test using V79 Chinese hamster cells, or in an in vivo bone marrow micronucleus test in mice after intravenous injection at doses up to 4 mg/kg (12 mg/m^2).

Fertility studies have not been conducted with motixafortide. No histopathological evidence of toxicity to male or female reproductive organs was observed in 28-day repeat-dose toxicity studies in rats and dogs.

14 CLINICAL STUDIES

The efficacy of APHEXDA in combination with filgrastim was evaluated in the GENESIS study (NCT 03246529). In this randomized, double-blind, placebo-controlled study, 122 patients with multiple myeloma were randomized in a 2:1 ratio to receive APHEXDA 1.25 mg/kg subcutaneously (N=80) or placebo (N=42). Prior to receiving APHEXDA or placebo, patients received daily morning doses of filgrastim 10-15 mcg/kg for 4 days. On the evening of Day 4, patients received APHEXDA or placebo. On Day 5, patients received a fifth morning dose of filgrastim within 1 hour prior to their first apheresis (12 hours ± 2 hours from the APHEXDA/placebo administration). The apheresis cell collection goal for the study was ≥ 6 × 10^6 CD34+ cells/kg. The assessment of CD34+ cells was performed by central and local laboratories. Central laboratory assessments were used for the efficacy results. Local laboratory results were used for clinical treatment decisions.

In the event that the cell collection goal was not achieved with the first apheresis on Day 5, patients received another morning dose of filgrastim on Day 6 within 1 hour prior to their second apheresis. In the event that the cell collection goal was still not achieved, patients received a second administration of APHEXDA or placebo on the evening of Day 6 and a seventh dose of filgrastim in the morning of Day 7 within 1 hour prior to a third apheresis. If the collection goal was not achieved, patients received an eighth dose of filgrastim in the morning of Day 8 within 1 hour prior to a fourth apheresis.

The median age of the study population was 63 years (range 34-75); 65% were males; 86% Caucasian, 8% African American, 2% Asian and 10% were of Hispanic or Latino ethnicity. Seventy percent of patients were previously treated with lenalidomide.

The efficacy of APHEXDA was based upon the proportion of patients who achieved a cell collection goal of ≥ 6 × 10^6 CD34+ cells/kg in up to 2 aphereses after administration of filgrastim and a single administration of APHEXDA or placebo.

Efficacy results showed that 67.5% of patients in the APHEXDA treatment arm versus 9.5% in the placebo arm achieved the cell collection goal of ≥ 6 × 10^6 CD34+ cells/kg in up to 2 aphereses after a single administration of APHEXDA or placebo, resulting in an adjusted difference between treatment arms of 56.8% (p < 0.0001) (Table 3).

Table 3: Proportion of Patients Who Achieved CD34+ Cell Collection Goal Following Single Administration of APHEXDA or Placebo (GENESIS)
Cell Collection Goal | APHEXDA and Filgrastim (N = 80) | Placebo and Filgrastim (N = 42) | p-value [The reported p values are two sided based on the Cochran-Mantel-Haenszel common proportion difference method stratifying for response status (CR or PR) at baseline and to baseline platelet count (<200 × 10^9/L or ≥ 200 × 10^9/L).]
Proportion of patients with ≥ 6 × 10^6 CD34+ cells/kg in up to 2 aphereses – Central laboratory | 67.5% | 9.5% | <0.0001
Proportion of patients with ≥ 6 × 10^6 CD34+ cells/kg in 1 apheresis – Central laboratory | 63.8% | 2.4% | <0.0001
Proportion of patients with ≥ 2 × 10^6 CD34+ cells/kg in 1 apheresis – Central laboratory | 87.5% | 38.1% | <0.0001

Multiple factors can influence time to engraftment and graft durability following stem cell transplantation. In the GENESIS study, time to neutrophil and platelet engraftment and graft durability following transplantation were similar across treatment groups.

16 HOW SUPPLIED/STORAGE AND HANDLING

APHEXDA (motixafortide) for injection is supplied as a white to off-white lyophilized powder in a single-dose vial for reconstitution. Each vial delivers 62 mg motixafortide free base.

NDC 73441-062-01 (Carton containing one vial)

STORAGE AND HANDLING

Store at 2°C to 8°C (36°F to 46°F) in original carton to protect from light.

- Discard prepared reconstituted solution after 24 hours storage under refrigeration 2°C to 8°C (36°F to 46°F) or at room temperature 20°C to 25°C (68°F to 77°F) protected from light.

17 PATIENT COUNSELING INFORMATION

- Advise patients of the risk of anaphylactic and hypersensitivity reactions (such as pruritus, flushing, urticaria, rash, vomiting, nausea and chills) during and after APHEXDA injection and to immediately report such signs and symptoms to healthcare professionals [see Warnings and Precautions (5.1)].
- Advise patients that APHEXDA may cause injection site reactions, such as pain, redness, and swelling [see Warnings and Precautions (5.2), Adverse Reactions (6.1, 6.2)].
- Advise females of reproductive potential to use effective contraceptive methods during APHEXDA treatment and for 8 days after the administration of APHEXDA [see Warnings and Precautions (5.6), Use in Specific Populations (8.1, 8.3)].
- Advise females of reproductive potential of the potential risk to a fetus. Advise females to contact their healthcare provider if they become pregnant or if pregnancy is suspected during treatment with APHEXDA [see Warnings and Precautions (5.6), Use in Specific Populations (8.1, 8.3)].
- Advise women that breastfeeding is not recommended during treatment with APHEXDA and for 8 days following the last dose [see Use in Specific Populations (8.2)].

Manufactured for:
Ayrmid Pharma Ltd.
Dublin, Ireland

Distributed by:
Gamida Cell Inc.
Naples, FL 34102 USA

APHEXDA® is a registered trademark of Ayrmid Pharma Ltd.
© Ayrmid Pharma, Ltd. All rights reserved.

PRINCIPAL DISPLAY PANEL - 62 mg Vial Carton

NDC 73441-062-01

APHEXDA®
motixafortide
for injection
62 mg per vial

For Subcutaneous Injection by
a Healthcare Provider Only
One single-dose vial
Discard unused solution

Rx Only